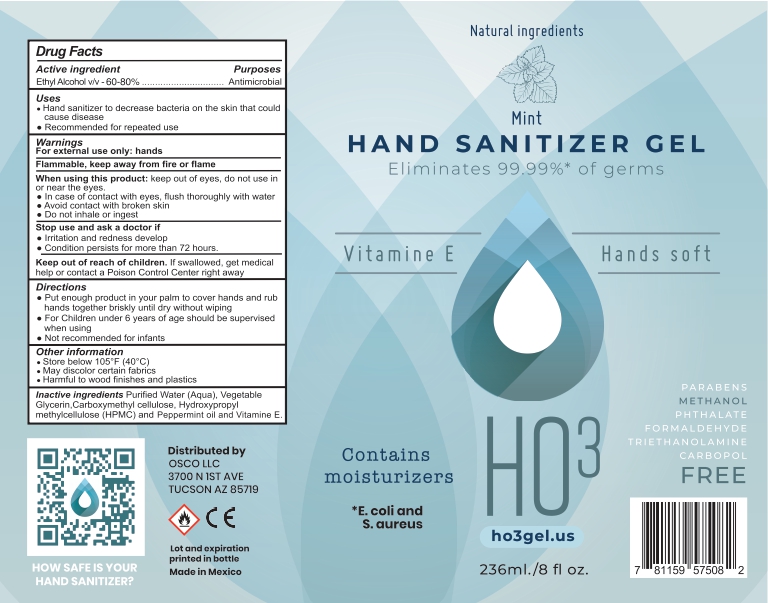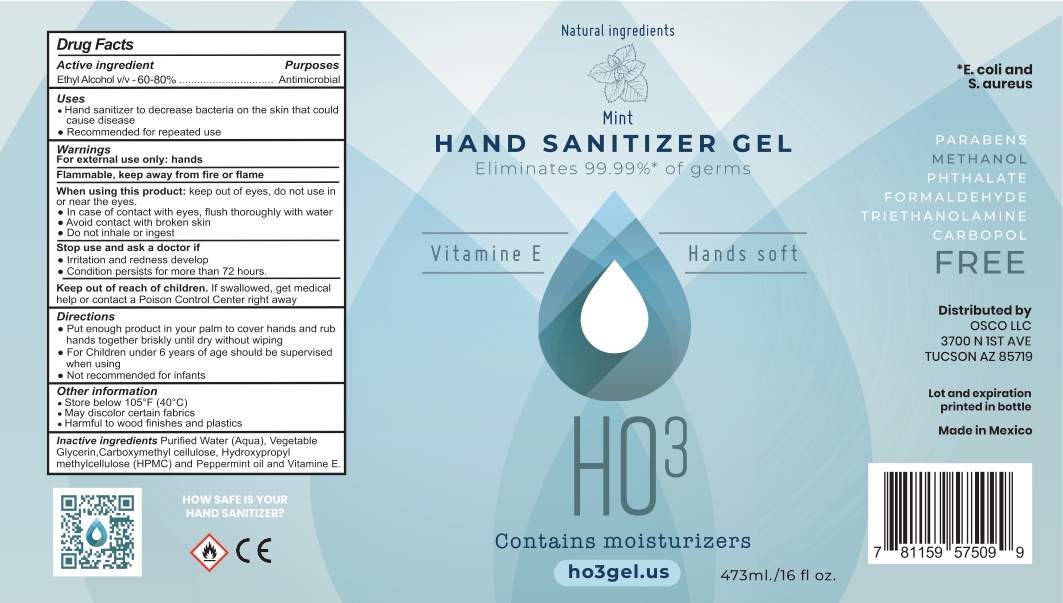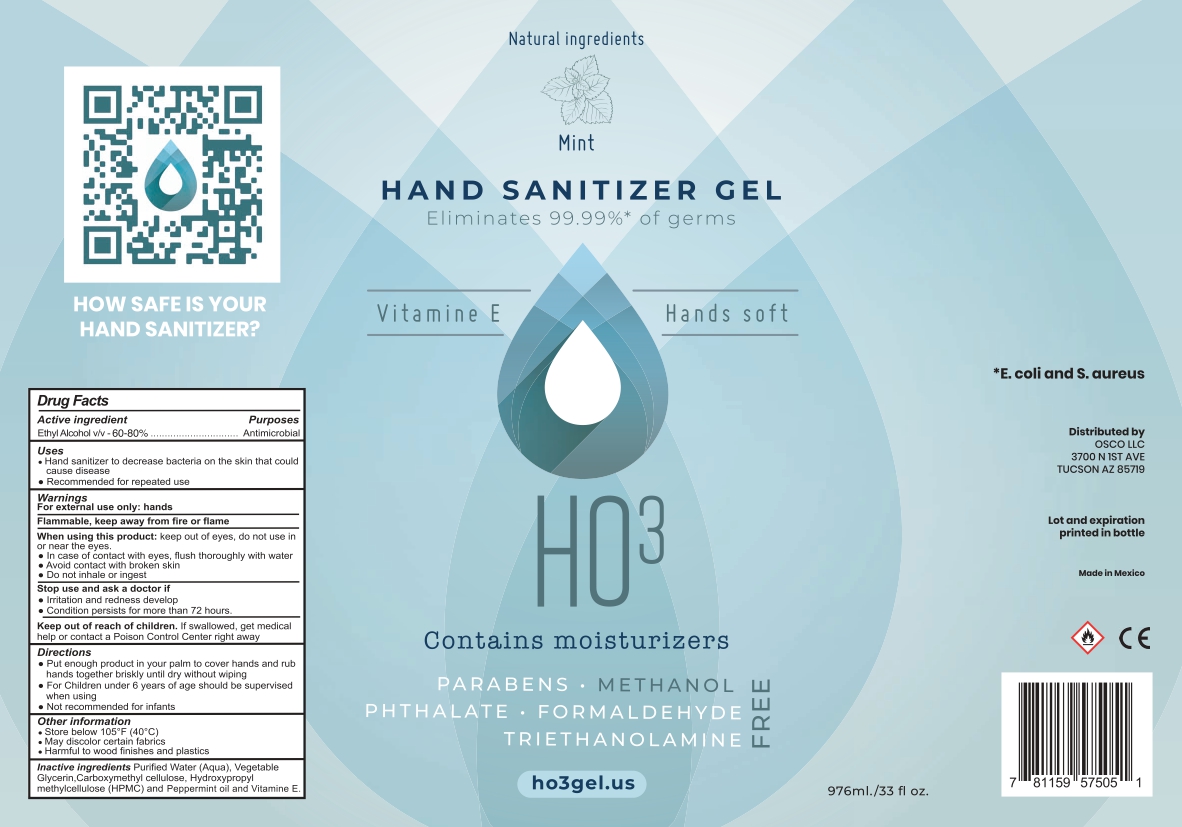 DRUG LABEL: HAND SANITIZER
NDC: 80535-0001 | Form: GEL
Manufacturer: FARMACIA SAN ARCANGEL, S.A. DE C.V.
Category: otc | Type: HUMAN OTC DRUG LABEL
Date: 20200907

ACTIVE INGREDIENTS: ALCOHOL 65 mL/100 mL
INACTIVE INGREDIENTS: CARBOXYMETHYLCELLULOSE; FD&C BLUE NO. 1; HYPROMELLOSE 2208 (60000 MPA.S); WATER; GLYCERIN; .ALPHA.-TOCOPHEROL ACETATE; PEPPERMINT OIL

Active Ingredient

Ethyl alcohol v/v- 60-80%

Purposes

Antimicrobial

Uses

Hand sanitizer to decrease bacteria on the skin that could cause disease

Recommended for repetead use

Warnings

For external use only: hands

Flammable, keep away form fire and flame

When using this product

keep out of ayes, do not use in or near the eyes

In case of contact with eyes, flush thorougly with water

Avoid contact with broken skin

Do not inhale or ingest

When using this product

keep out of ayes, do not use in or near the eyes

In case of contact with eyes, flush thorougly with water

Avoid contact with broken skin

Do not inhale or ingest

Stop use and ask a doctor if

Irritation and redness develop

Condition persists for more than 72 hours

Keep out of reach of children

If swallowed, get medical help or contact a poison center right away

Directions

Put enough product in your palm to cover hands and rub hands together briskly until dry without wiping

for children under 6 years of age should be supervised when using

not recommended for infants

Other information

Store below 105 F 40C

Mary discolour certain fabrics

harmful to wood finishes and plastics

Inactive ingredients

Purified water (aqua), vegetable glycerin, carboxymethyl cellulose, hydroxypropyl methylcellulose HPMC, and pepper mint oild and vitamine E

Principal display

Natural ingredients

Mint

Hand sanitizer gel

eliminates 99.9% of germs

vitamine E hands soft

contain mosturizers

*e coli and S. areus

HO3

parabens

methanol

formaldehyde

triethanolamine

carbopol

free